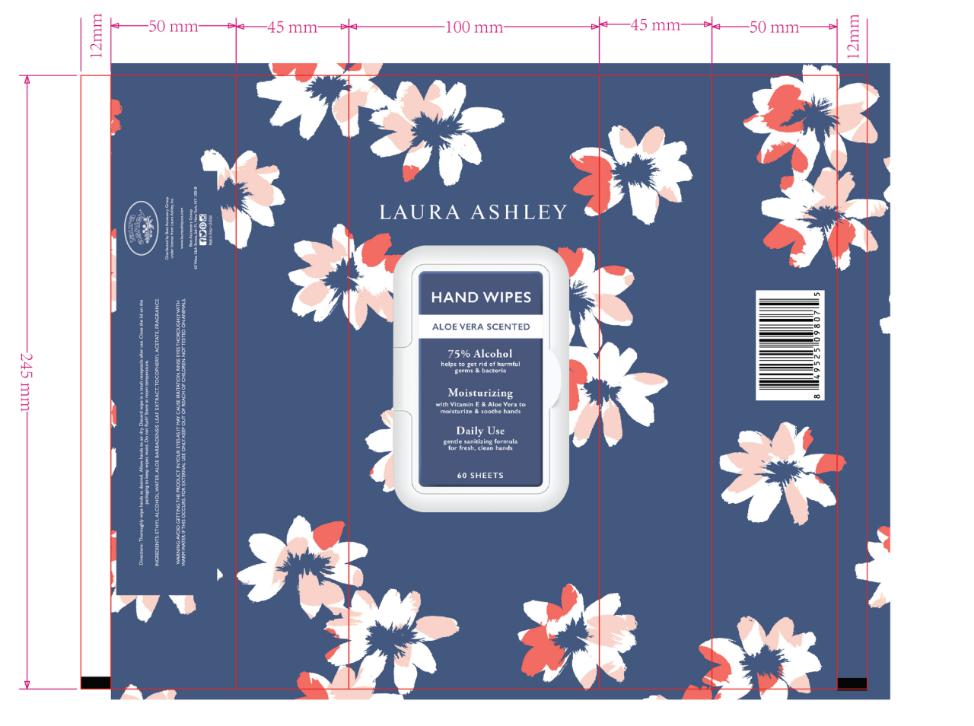 DRUG LABEL: HAND WIPES ALOE VERA SCENTED 75% ALCOHOL
NDC: 78936-019 | Form: SWAB
Manufacturer: Hangzhou Caring Cleaning Commodity Co.,Ltd
Category: otc | Type: HUMAN OTC DRUG LABEL
Date: 20201016

ACTIVE INGREDIENTS: ALCOHOL 0.75 g/1 1
INACTIVE INGREDIENTS: ALOE VERA LEAF; ALPHA-TOCOPHEROL ACETATE; WATER; FRAGRANCE FLORAL ORC0902236

HAND WIPES ALOE VERA SCENTED 75% ALCOHOL

Active Ingredient(s)

Alcohol 75%

Purpose

Antiseptic

Use

Decreases bacteria on hands

Warnings

For external use only.

Flammable, keep away from fire or flame.

When using this product

Avoid contact with eyes; in case of contact, flush eyes with water

Stop use and ask a doctor if irritation or redness develops and persists.

Keep out of reach of children. If swallowed, get medical help or contact a Poison Control Center right away.

Directions

Wet hands thoroughly with product and allow to dry

Inactive ingredients

Water,Aloe Barbadensis Leaf Extract,Tocopheryl Acetate,Fragrance

Package Label - Principal Display Panel

60 SWAB IN 1 BAG NDC: 78936-019-01